DRUG LABEL: Oxygen
NDC: 57728-0001 | Form: GAS
Manufacturer: Atlantic Medical Inc.
Category: prescription | Type: HUMAN PRESCRIPTION DRUG LABEL
Date: 20091117

ACTIVE INGREDIENTS: Oxygen 99 L/100 L

Oxygen